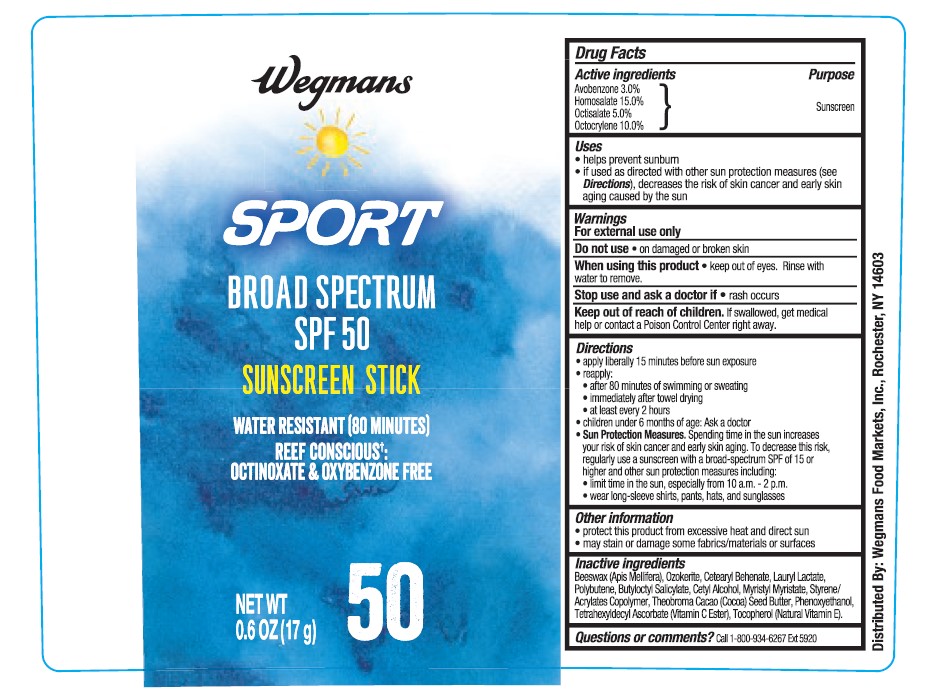 DRUG LABEL: Wegmans Sport Sunscreen Stick SPF 50
NDC: 47124-127 | Form: STICK
Manufacturer: WEGMANS FOOD MARKETS INC
Category: otc | Type: HUMAN OTC DRUG LABEL
Date: 20241016

ACTIVE INGREDIENTS: AVOBENZONE 30 mg/1 g; HOMOSALATE 150 mg/1 g; OCTISALATE 50 mg/1 g; OCTOCRYLENE 100 mg/1 g
INACTIVE INGREDIENTS: WHITE WAX; .ALPHA.-TOCOPHEROL, DL-; BUTYLOCTYL SALICYLATE; CETYL ALCOHOL; MYRISTYL MYRISTATE; COCOA BUTTER; PHENOXYETHANOL; TETRAHEXYLDECYL ASCORBATE; CERESIN; STEARYL BEHENATE; LAURYL LACTATE; POLYBUTENE (1400 MW)

Wegmans Sport Sunscreen Stick SPF 50

Active Ingredients

Avobenzone 3.0%, Homosalate 15.0%, Octisalate 5.0%, Octocrylene 10.0%

Purpose

Sunscreen

Uses

- helps prevent sunburn
- if used as directed with other sun protection measures (see Directions), decreases the risk of skin cancer and early skin aging caused by the sun

Warnings

For external use only

Do not use

• on damaged or broken skin.

When using this product

• keep out of eyes. Rinse with water to remove.

Stop use and ask a doctor if

• rash occurs.

Keep out of reach of children.

If swallowed, get medical help or contact a Poison Control Center right away.

Directions

- apply liberally 15 minutes before sun exposure
- reapply:

• after 80 minutes of swimming or sweating

• immediately after towel drying

• at least every 2 hours

- children under 6 months of age: Ask a doctor
- Sun Protection Measures. Spending time in the sun increases your risk of skin cancer and early skin aging. To decrease this risk, regularly use a sunscreen with a Broad Spectrum SPF value of 15 or higher and other sun protection measures including:

• limit time in the sun, especially from 10 a.m. - 2 p.m.

• wear long-sleeved shirts, pants, hats, and sunglasses

Other Information

- protect the product in this container from excessive heat and direct sun
- may stain or damage some fabrics, materials or surfaces

Inactive Ingredient(s)

beeswax, ozokertie, cetearyl behenate, lauryl lactate, polybutene, butyloctyl salicylate, cetyl alcohol, myristyl myristate, styrene/acrylates copolymer, theobroma cacao (cocoa) seed butter, phenoxyethanol, tetrahexyldecyl ascorbate (vitamin C ester), tocopherol (vitamin E).